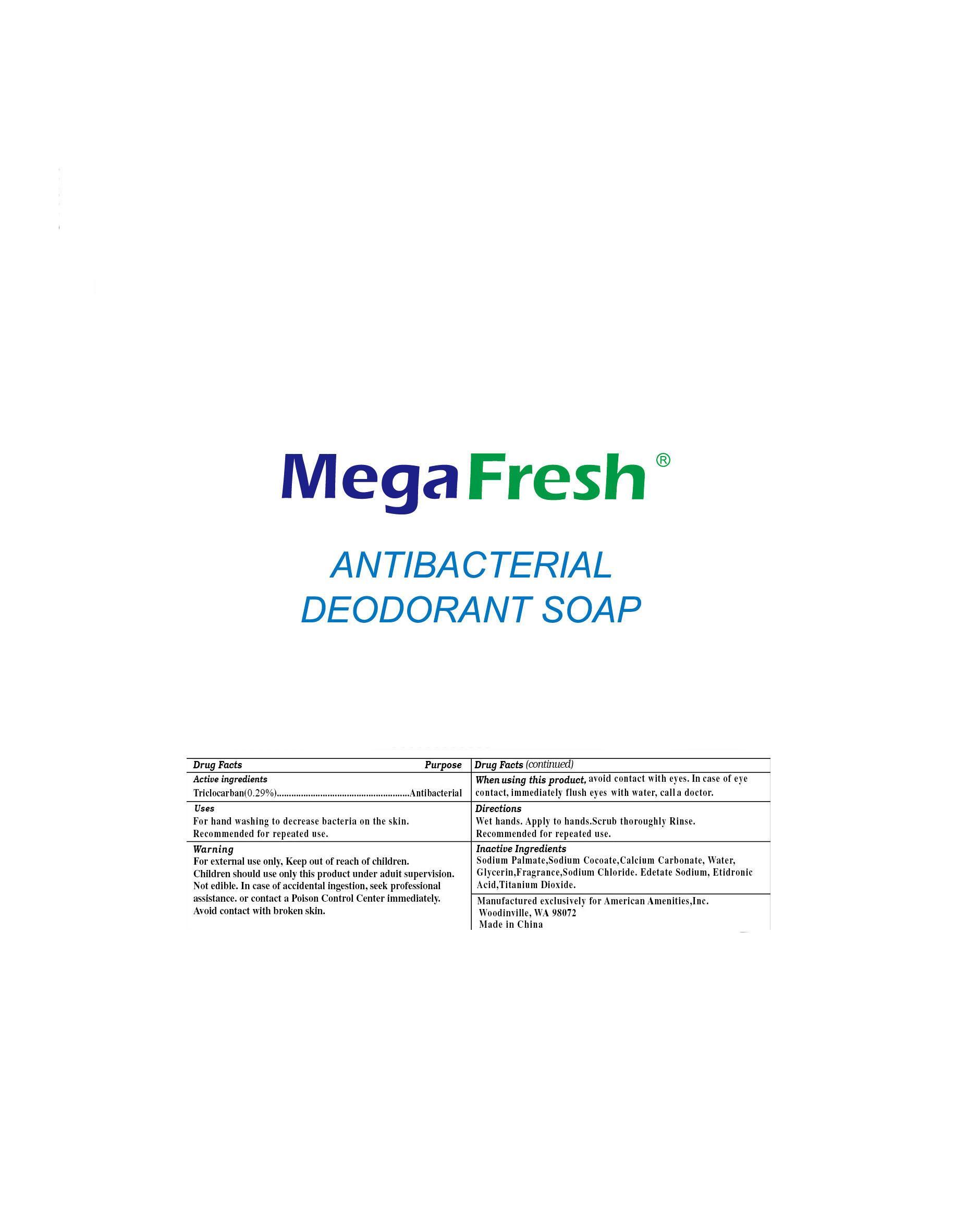 DRUG LABEL: DEODORANT 
NDC: 53507-001 | Form: SOAP
Manufacturer: Shanghai Kangyi Tourism Products Co., Ltd. 
Category: otc | Type: HUMAN OTC DRUG LABEL
Date: 20140526

ACTIVE INGREDIENTS: TRICLOCARBAN 0.29 g/100 g
INACTIVE INGREDIENTS: WATER; Sodium Palmate; Sodium Cocoate; Calcium Carbonate; Glycerin; Sodium Chloride; Edetate Sodium; Etidronic Acid; Titanium Dioxide

MegaFresh Deodorant Soap

Active Ingredient

Triclocarban 0.29%

PURPOSE

Antibacterial

Use

For hand washing to decrease bacteria on the skin. Recommended for repeated use.

WARNINGS

For external use only. Keep out of reach of children.

Children should use only this product under adult supervision.

Not edible. In case of accidental ingestion, seek professional assistance or contact a Poison Control Center immediately.

Avoid contact with broken skin.

When using this product, avoid contact with eyes. In case of eye contact, immediately flush eyes with water, call a doctor.

keep out of reach of children

Directions

Wet hands. Apply to hands. Scrub thoroughly. Rinse.

Recommended for repeated use.

Inactive ingredients

Sodium Palmate, Sodium Cocoate, Calcium Carbonate, Water, Glycerin, Fragrance, Sodium Chloride, Edetate Sodium, Etidronic Acid, Titanium Dioxide.